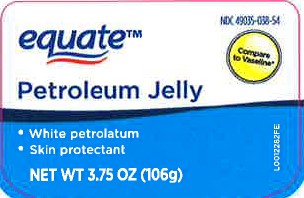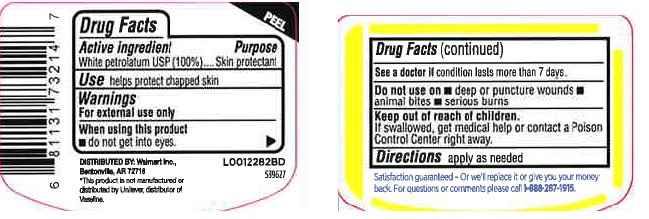 DRUG LABEL: Petroleum Skin Protectant
NDC: 49035-038 | Form: JELLY
Manufacturer: Walmart Inc.
Category: otc | Type: HUMAN OTC DRUG LABEL
Date: 20260227

ACTIVE INGREDIENTS: PETROLATUM 1 g/1 g

Equate 069.001/AA
Petroleum Jelly

Active ingredient

White petrolatum USP (100%)

Purpose

Skin protectant

Uses

- helps protect chapped skin

Warnings

For external use only

When using this product

- do not get into eyes

See a doctor if

condition lasts more than 7 days

Do not use on

- deep or puncture wounds
- animal bites
- serious burns

Keep out of reach of children.

If swallowed, get medical help or contact a Poison Control Center right away.

Directions

apply as needed

Inactive Ingredients

None

Dislcaimer

*This poduct is not manufactured or distributed by Unliever, distributor of Vaseline.

Adverse Reactions

DISTRIBUTED BY:

Walmart Inc.,

Bentonville, AR 72716

Satisfaction guaranteed - Or we'll replace it or give you your money back. For questions or comments please call 1-888-287-1915.

principal display panel

NDC 49035-038-54

equate™

Compare to Vaseline*

PETROLEUM JELLY

- White Petrolatum
- Skin Protectant

NET WT 3.75 OZ (106 g)